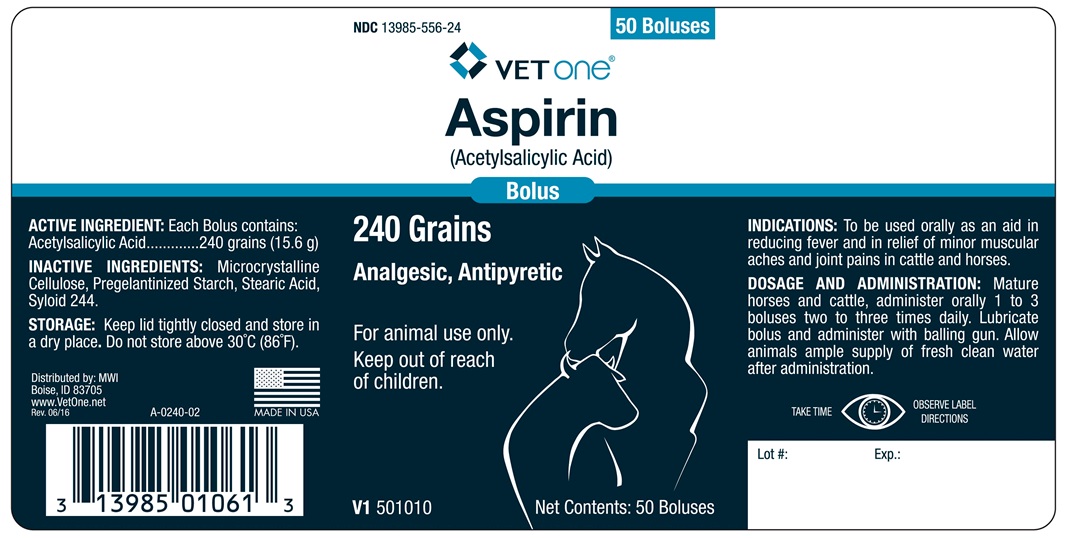 DRUG LABEL: ASPIRIN 
                        
                        
NDC: 13985-556 | Form: TABLET
Manufacturer: MWI Veterinary Supply, Inc.
Category: animal | Type: OTC ANIMAL DRUG LABEL
Date: 20170622

ACTIVE INGREDIENTS: ASPIRIN 15.6 g/1 1

ASPIRIN BOLUS

INDICATIONS AND USAGE

(Acetylsalicylic Acid)

240 Grains

Analgesic, Antipyretic

For animal use only.

Keep out of reach of children

INDICATIONS

To be used orally as an aid in reducing fever and in relief of minor muscular aches and joint pains in cattle and horses.

DOSAGE AND ADMINISTRATION

Mature Horses and Cattle, administer orally 1 to 3 Boluses two to three times daily. Lubricate bolus and administer with balling gun. Allow Animals ample supply of fresh clean water after administration.

ACTIVE INGREDIENT

Each bolus contains:

Acetylsalicylic Acid..........240 grains (15.6 g)

INACTIVE INGREDIENT

Microcrystalline Cellulose, Pregelantinized Starch, Stearic Acid, Syloid 244.

STORAGE AND HANDLING

Keep lid tightly closed and store in a dry place.

Do not store above 30oC (86oF).

TAKE TIME OBSERVE LABEL DIRECTIONS